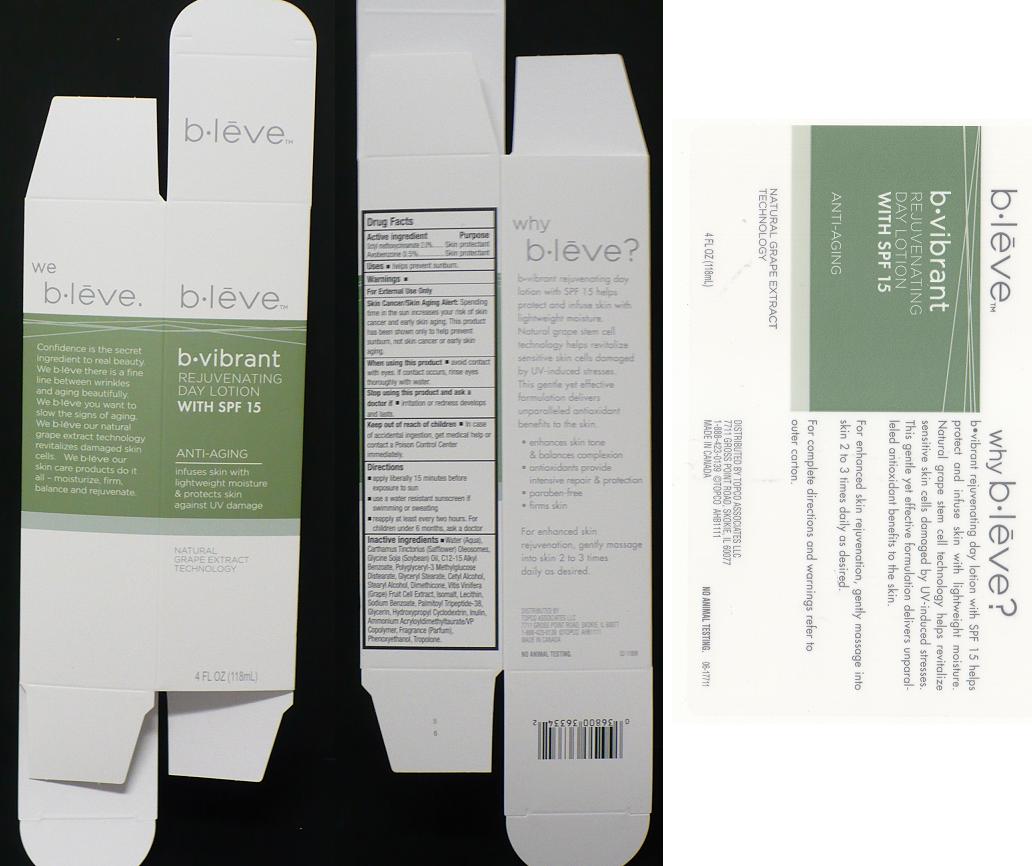 DRUG LABEL: bleve
NDC: 36800-353 | Form: LOTION
Manufacturer: TOPCO ASSOCIATES LLC
Category: otc | Type: HUMAN OTC DRUG LABEL
Date: 20120320

ACTIVE INGREDIENTS: OCTINOXATE 2 mL/100 mL; AVOBENZONE 0.5 mL/100 mL
INACTIVE INGREDIENTS: WATER; CARTHAMUS TINCTORIUS (SAFFLOWER) OLEOSOMES; SOYBEAN OIL; ALKYL (C12-15) BENZOATE; POLYGLYCERIN-3; GLYCERYL MONOSTEARATE; CETYL ALCOHOL; STEARYL ALCOHOL; DIMETHICONE; VITIS VINIFERA FLOWERING TOP; ISOMALT; LECITHIN, SOYBEAN; SODIUM BENZOATE; PALMITOYL TRIPEPTIDE-5; GLYCERIN; HYDROXYPROPYLBETADEX (0.58-0.68 MS); INULIN; CARBOMER COPOLYMER TYPE A; PHENOXYETHANOL; TROPOLONE

DRUG FACTS

ACTIVE INGREDIENT

OCTYL METHOXYCINNAMATE 2%

AVOBENZONE 0.5%

PURPOSE

SKIN PROTECTANT

SKIN PROTECTANT

USES

HELPS PREVENT SUNBURN.

WARNINGS

FOR EXTERNAL USE ONLY.

SKIN CANCER/SKIN AGING ALERT

SPENDING TIME IN THE SUN INCREASES YOUR RISK OF SKIN CANCER AND EARLY SKIN AGING. THIS PRODUCT HAS BEEN SHOWN ONLY TO HELP PREVENT SUNBURN, NOT SKIN CANCER OR EARLY SKIN AGING.

WHEN USING THIS PRODUCT

AVOID CONTACT WITH EYES. IF CONTACT OCCURS, RINSE EYES THOROUGHLY WITH WATER.

STOP USING THIS PRODUCT AND ASK A DOCTOR IF

IRRITATION OR REDNESS DEVELOPS AND LASTS.

KEEP OUT OF REACH OF CHILDREN

IN CASE OF ACCIDENTAL INGESTION, GET MEDICAL HELP OR CONTACT A POISON CONTROL CENTER IMMEDIATELY.

DIRECTIONS

APPLY LIBERALLY 15 MINUTES BEFORE EXPOSURE TO SUN. USE A WATER RESISTANT SUNSCREEN IF SWIMMING OR SWEATING. REAPPLY AT LEAST EVERY TWO HOURS. FOR CHILDREN UNDER 6 MONTHS, ASK A DOCTOR.

INACTIVE INGREDIENTS

WATER (AQUA), CARTHAMUS TINCTORIUS (SAFFLOWER) OLEOSOMES, GLYCINE SOJA (SOYBEAN) OIL, C12-15 ALKYL BENZOATE, POLYGLYCERYL-3 METHYLGLUCOSE DISTEARATE, GLYCERYL STEARATE, CETYL ALCOHOL, STEARYL ALCOHOL, DIMETHICONE,VITIS VINIFERA (GRAPE) FRUIT CELL EXTRACT, ISOMALT, LECITHIN, SODIUM BENZOATE, PALMITOYL TRIPEPTIDE-38, GLYCERIN, HYDROXYPROPYL CYCLODEXTRIN, INULIN, AMMONIUM ACRYLOYLDIMETHYLTAURATE/VP COPOLYMER, FRAGRANCE (PARFUM), PHENOXYETHANOL, TROPOLONE.